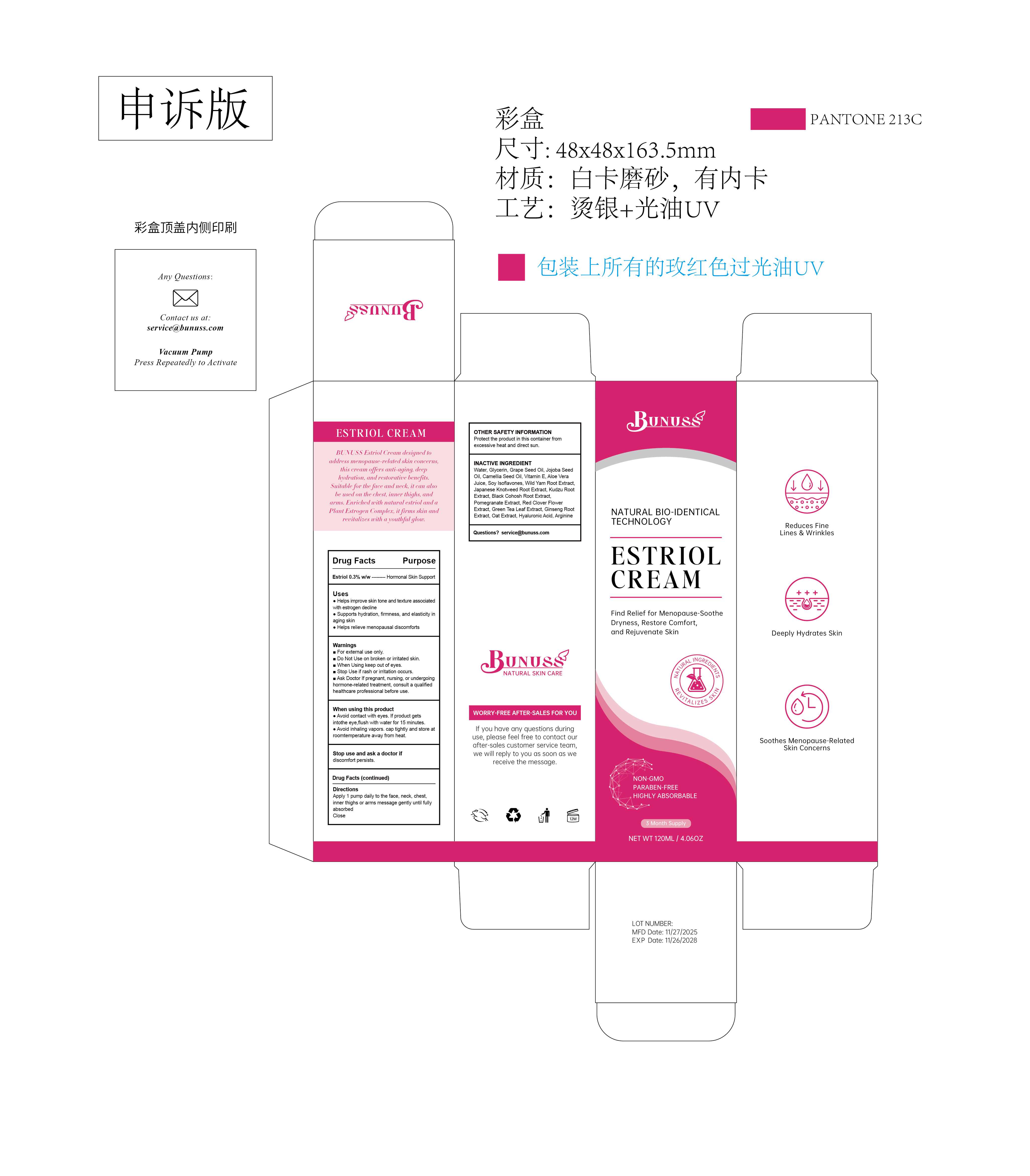 DRUG LABEL: BUNUSS Estriol Face
NDC: 84867-024 | Form: CREAM
Manufacturer: Jiashen International Trade Limited
Category: otc | Type: HUMAN OTC DRUG LABEL
Date: 20260104

ACTIVE INGREDIENTS: ESTRIOL 3 g/100 mL
INACTIVE INGREDIENTS: CAPRYLYL GLYCOL; CARBOMER; RED CLOVER; WATER; SOY ISOFLAVONES; GREEN TEA LEAF; SQUALANE; COCOS NUCIFERA (COCONUT) OIL; AVENA SATIVA (OAT) BRAN; ARGININE; POMEGRANATE; ALOE BARBADENSIS LEAF JUICE; PANAX GINSENG ROOT OIL; BUTYLENE GLYCOL; CETEARYL ALCOHOL; GLYCERIN; PUERARIA MIRIFICA ROOT; CIMICIFUGA RACEMOSA ROOT; SIMMONDSIA CHINENSIS (JOJOBA) SEED OIL; TOCOPHEROL; CITRUS AURANTIUM DULCIS (ORANGE) PEEL POWDER; HYALURONIC ACID; SHEA BUTTER; POLYGONUM CUSPIDATUM ROOT; PUERARIA MONTANA VAR. LOBATA ROOT; 1,2-HEXANEDIOL

84867-024-01 BUNUSS Estriol Face Cream

ACTIVE INGREDIENT

Estriol 0.3% w/w --------- Hormonal Skin Support

Uses
Helps improve skin tone and texture associated with estrogen decline Supports hydration, firmness, and elasticity in aging skin
Helps relieve menopausal discomforts

Keep out of children to reach

Warnings
For external use only.
Do Not Use on broken or irritated skin.
When Using keep out of eyes.
Stop Use if rash or irritation occurs.
Ask Doctor If pregnant, nursing, or undergoing hormone-related treatment, consult a qualifiedhealthcare professional before use.

DOSAGE AND ADMINISTRATION

Apply1 pump daily to the face, neck, chest,inner thighs or arms message gently until fully absorbed
Close

INDICATIONS AND USAGE

When using this productAvoid contact with eyes. If product gets intothe eye,flush with water for 15 minutes.Avoid inhaling vapors. cap tightly and store atroomtemperature away from heat.

INACTIVE INGREDIENT

INACTIVE INGREDIENTWater, Glycerin, Grape Seed Oil, Jojoba SeedOil, Camellia Seed Oil, Vitamin E, Aloe Vera Juice, Soy Isoflavones, Wild Yam Root Extract.Japanese Knotweed Root Extract, Kudzu RootExtract, Black Cohosh Root Extract,Pomegranate Extract, Red Clover Flower Extract, Green Tea Leaf Extract, Ginseng Root Extract, Oat Extract, Hyaluronic Acid, Arginine